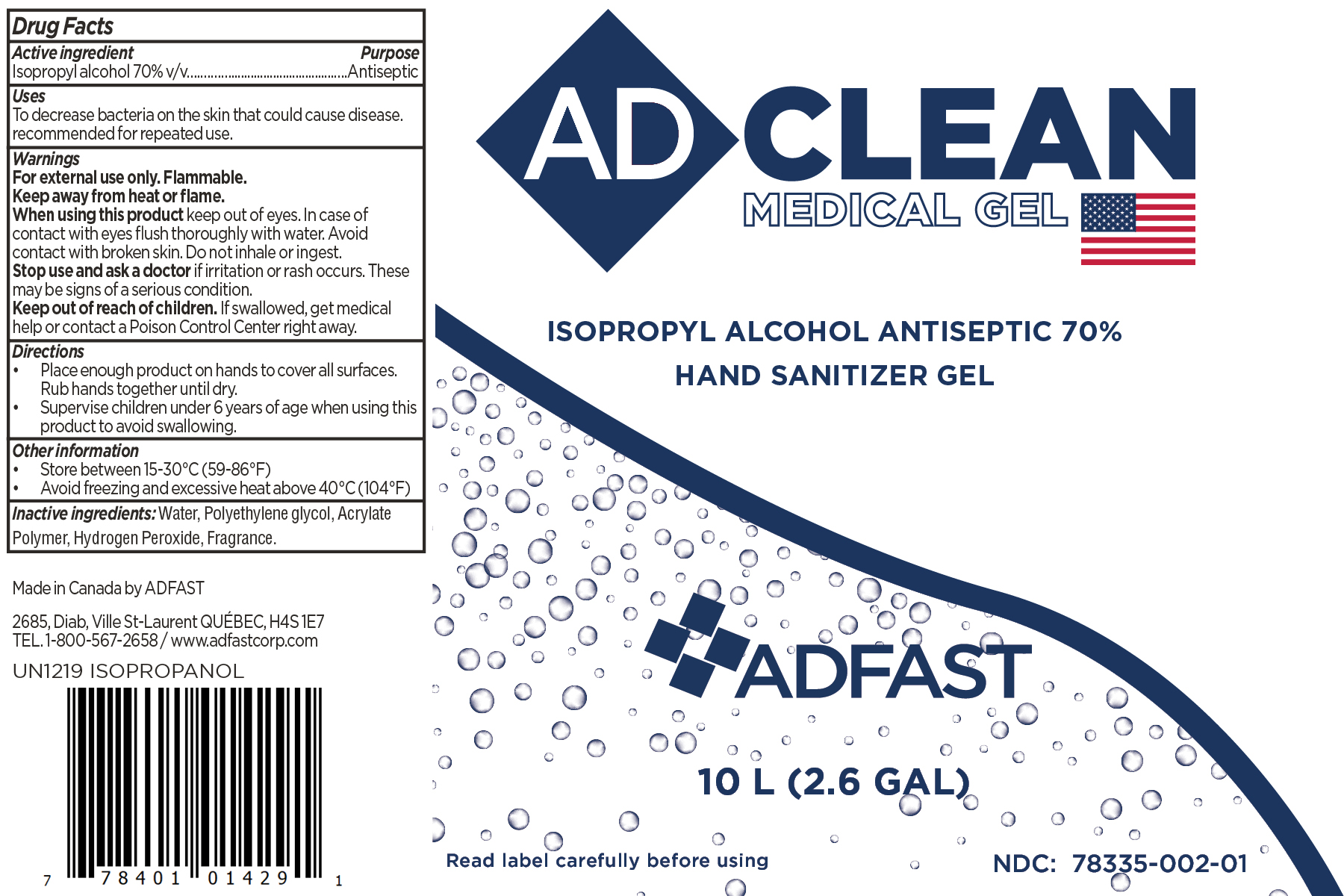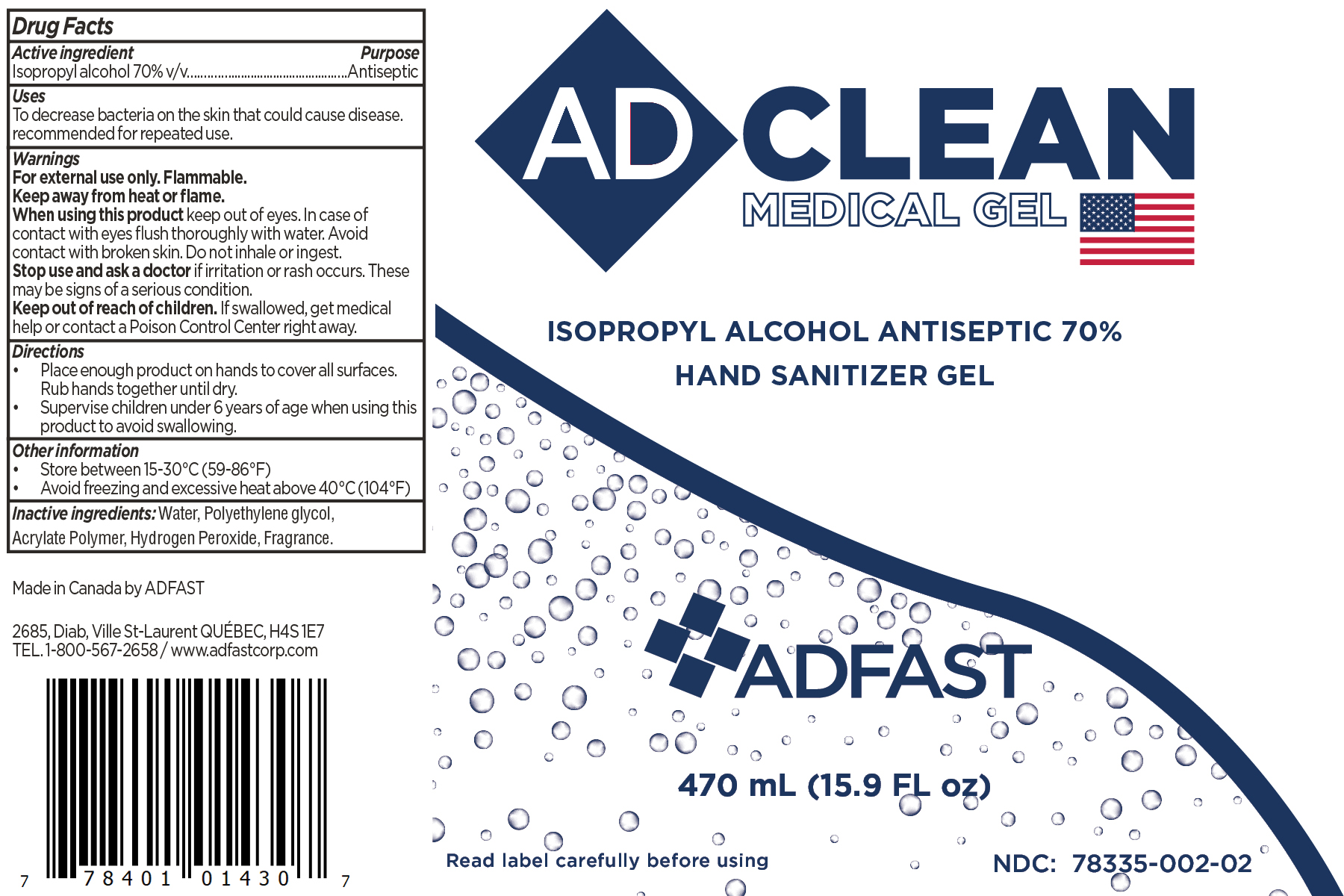 DRUG LABEL: ADCLEAN Medical Gel
NDC: 78335-002 | Form: GEL
Manufacturer: Adfast Corp
Category: otc | Type: HUMAN OTC DRUG LABEL
Date: 20220125

ACTIVE INGREDIENTS: ISOPROPYL ALCOHOL 70 mL/100 mL
INACTIVE INGREDIENTS: RAPIDGEL EZ1 3 mL/100 mL; HYDROGEN PEROXIDE 0.45 mL/100 mL; WATER 26.25 mL/100 mL; FRAGRANCE LEMON ORC2001060 0.3 mL/100 mL

ADCLEAN Medical Gel

This is a hand sanitizer manufactured according to the Temporary Policy for Preparation of Certain Alcohol-Based Hand Sanitizer Products During the Public Health Emergency (CoViD-19); Guidance for Industry.

The hand sanitizer is manufactured using only the following United States Pharmacopoeia (USP) grade ingredients in the preparation of the product (percentage in final product formulation) consistent with World Health Organization (WHO) recommendations:

1. Isopropyl Alcohol (70%, v/v) in an aqueous solution denatured according to Alcohol and Tobacco Tax and Trade Bureau regulations in 27 CFR part 20.
2. Purified water = 26.25 v%
3. Rapidgel EZ1 = 3.00 v%
4. Hydrogen peroxide 29% = 0.45 v%
5. Fragrance = 0.30 v%

The firm does not add other active or inactive ingredients. Different or additional ingredients may impact the quality and potency of the product.

Active Ingredient(s)

Isopropyl Alcohol 70% v/v. Purpose: Antiseptic

Purpose

Antiseptic, Hand Sanitizer

Use

Hand Sanitizer to help reduce bacteria that potentially can cause disease.

Warnings

For external use only. Flammable. Keep away from heat or flame

Do not use

- on children less than 2 months of age
- on open skin wounds

When using this product keep out of eyes, ears, and mouth. In case of contact with eyes, rinse eyes thoroughly with water.
Stop use and ask a doctor if irritation or rash occurs. These may be signs of a serious condition.
Keep out of reach of children. If swallowed, get medical help or contact a Poison Control Center right away.

Stop use and ask a doctor if irritation or rash occurs. These may be signs of a serious condition.

Keep out of reach of children. If swallowed, get medical help or contact a Poison Control Center right away.

Directions

- Place enough product on hands to cover all surfaces. Rub hands together until dry.
- Supervise children under 6 years of age when using this product to avoid swallowing.

Other information

- Store between 15-30C (59-86F)
- Avoid freezing and excessive heat above 40C (104F)

Inactive ingredients

Water

Polyethylene Glycol

Acrylate Polymer

Hydrogen Peroxide

Fragrance

Package Label - Principal Display Panel

78335-002